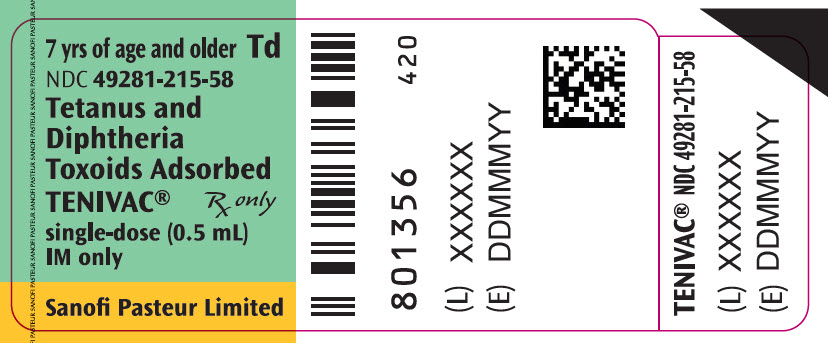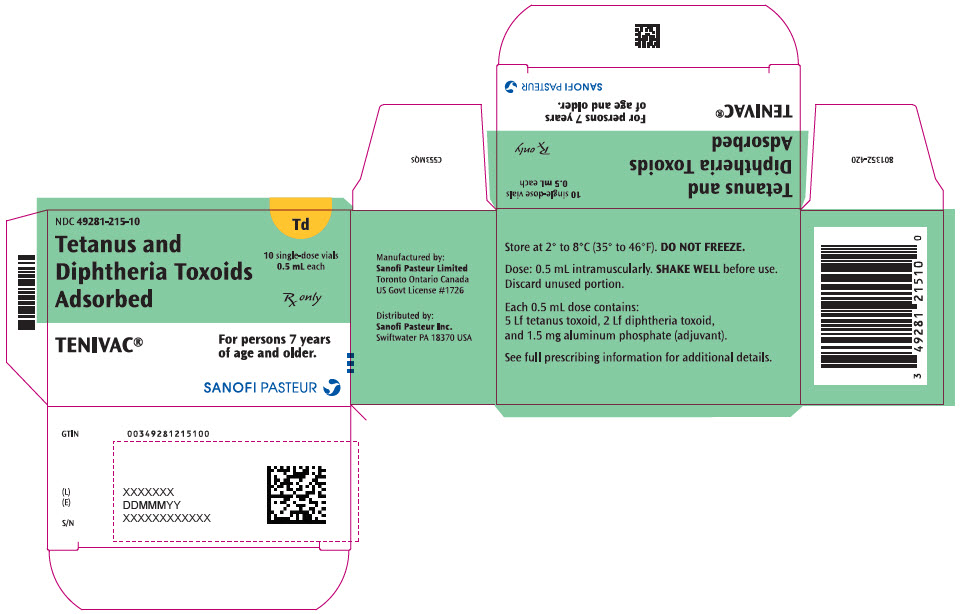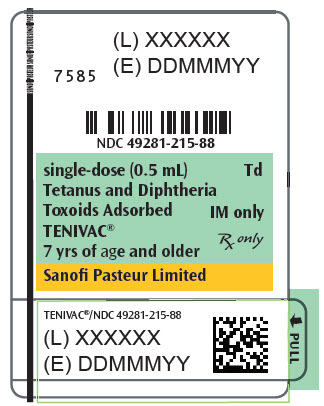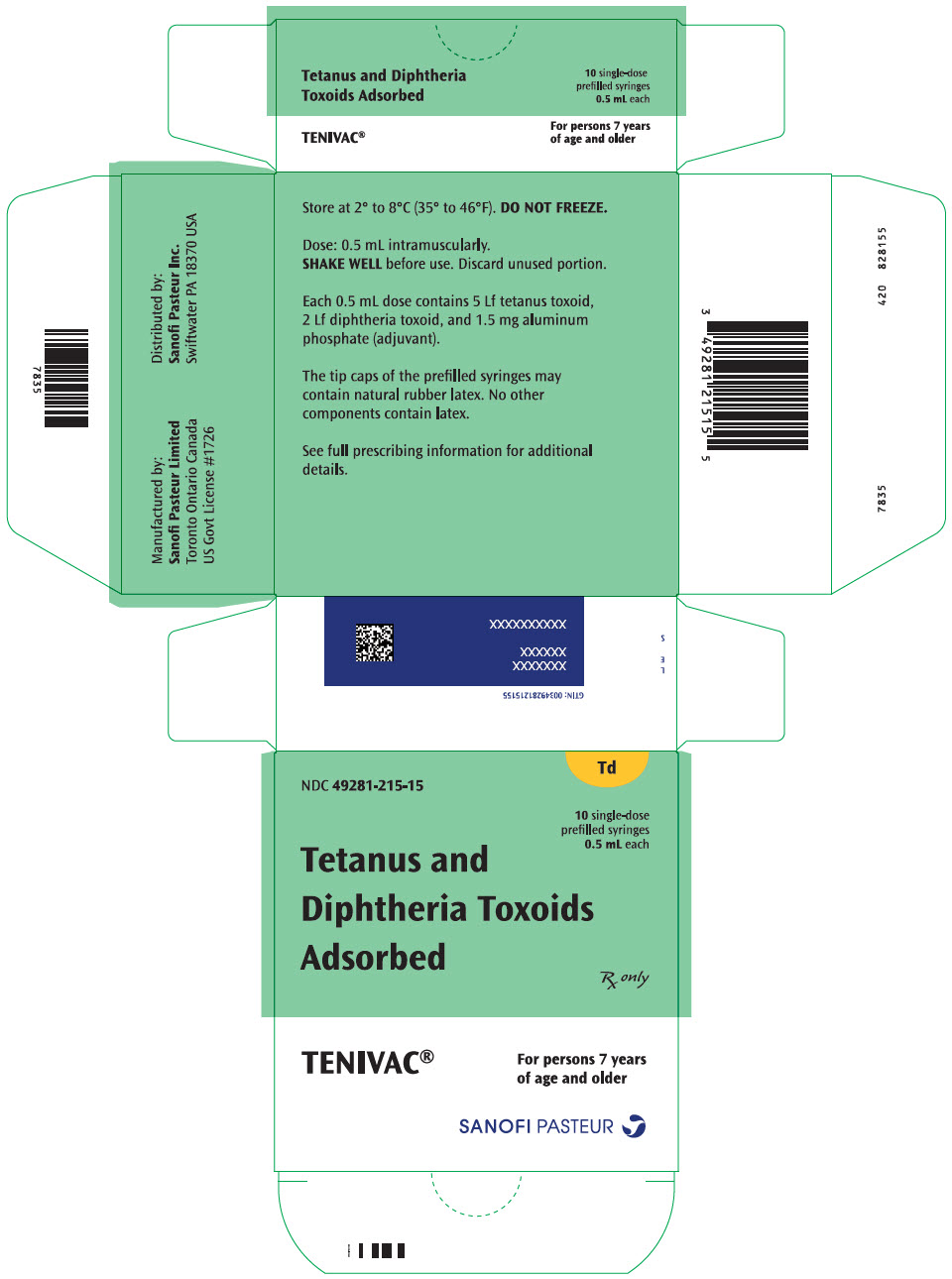 DRUG LABEL: TENIVAC
NDC: 49281-215 | Form: INJECTION, SUSPENSION
Manufacturer: Sanofi Pasteur Inc.
Category: other | Type: VACCINE LABEL
Date: 20240412

ACTIVE INGREDIENTS: CLOSTRIDIUM TETANI TOXOID ANTIGEN (FORMALDEHYDE INACTIVATED) 5 [Lf]/0.5 mL; CORYNEBACTERIUM DIPHTHERIAE TOXOID ANTIGEN (FORMALDEHYDE INACTIVATED) 2 [Lf]/0.5 mL
INACTIVE INGREDIENTS: ALUMINUM PHOSPHATE 1.5 mg/0.5 mL; FORMALDEHYDE

HIGHLIGHTS OF PRESCRIBING INFORMATION

These highlights do not include all the information needed to use TENIVAC® safely and effectively. See full prescribing information for TENIVAC.
TENIVAC (Tetanus and Diphtheria Toxoids Adsorbed)
Suspension for Intramuscular Injection
Initial U.S. Approval: 2003

1 INDICATIONS AND USAGE

TENIVAC is a vaccine indicated for active immunization for the prevention of tetanus and diphtheria in persons 7 years of age and older. (1)

2 DOSAGE AND ADMINISTRATION

- Each 0.5 mL dose should be administered intramuscularly. (2.5)
- Primary immunization with TENIVAC consists of 3 doses. The first 2 doses are administered 2 months apart and the third dose is administered 6-8 months after the second dose. (2.1)
- TENIVAC may be used for booster immunization against tetanus and diphtheria. Routine booster immunization against tetanus and diphtheria is recommended at 11-12 years of age and every 10 years thereafter. (2.2)
- For post-exposure diphtheria prophylaxis and for management of a tetanus prone wound, a booster dose of TENIVAC may be administered if at least 5 years have elapsed since previous receipt of a diphtheria toxoid and tetanus toxoid containing vaccine. (2.3) (2.4)

3 DOSAGE FORMS AND STRENGTHS

Suspension for injection supplied in 0.5 mL single-dose vials or syringes. (3)

4 CONTRAINDICATIONS

Severe allergic reaction (e.g., anaphylaxis) to a previous dose of TENIVAC, or any other tetanus or diphtheria toxoid-containing vaccine, or any component of this vaccine. (4.1)

5 WARNINGS AND PRECAUTIONS

- The tip caps of the prefilled syringes may contain natural rubber latex which may cause allergic reactions in latex sensitive individuals. (5.2)
- More frequent administration of TENIVAC than described in Dosage and Administration (2.1, 2.2, 2.3, 2.4) may be associated with increased incidence and severity of adverse reactions. (5.3)
- Persons who experienced an Arthus-type hypersensitivity reaction following a prior dose of a tetanus toxoid-containing vaccine should not receive TENIVAC more frequently than every 10 years, even for tetanus prophylaxis as part of wound management. (5.4)
- Carefully consider benefits and risks before administering TENIVAC to persons with a history of Guillain-Barré syndrome within 6 weeks of a previous tetanus toxoid-containing vaccine. (5.5)
- Syncope (fainting) has been reported following vaccination with TENIVAC. Procedures should be in place to avoid injury from fainting. (5.8)

6 ADVERSE REACTIONS

- The most frequent solicited injection site reaction within 0-3 days following TENIVAC was pain, reported in 78.3% of study participants 11-59 years of age and 35.3% of participants ≥60 years of age. (6.1)
- The most frequent solicited systemic reaction within 0-3 days following TENIVAC was headache, reported in 17.9% of participants, overall. (6.1)
- Other common (≥10%) solicited adverse reactions within 0-3 days following TENIVAC were injection site redness, injection site swelling, malaise, muscle weakness and pain in joints. (6.1)

To report SUSPECTED ADVERSE REACTIONS, contact Sanofi Pasteur Inc. at 1-800-822-2463 (1-800-VACCINE) or VAERS at 1-800-822-7967 or http://vaers.hhs.gov

7 DRUG INTERACTIONS

- No safety and immunogenicity data are available on the concomitant administration of TENIVAC with other US licensed vaccines. (7.1)
- If passive protection against tetanus is required, Tetanus Immune Globulin (TIG) (Human) may be administered concomitantly at a separate site with a separate needle and syringe. (7.2)
- Immunosuppressive therapies may reduce the immune response to TENIVAC. (7.3)

8 USE IN SPECIFIC POPULATIONS

Pre- and post-vaccination tetanus and diphtheria seroprotection rates were lower in study participants ≥65 years of age compared to younger participants. In general, rates of solicited adverse reactions were not higher in participants ≥65 years of age compared to younger participants. (8.5)

FULL PRESCRIBING INFORMATION

1 INDICATIONS AND USAGE

TENIVAC® is a vaccine indicated for active immunization for the prevention of tetanus and diphtheria in persons 7 years of age and older.

2 DOSAGE AND ADMINISTRATION

2.1 Primary Immunization

In persons who have not been immunized previously against tetanus and diphtheria, primary immunization with TENIVAC consists of three 0.5 mL doses. The first 2 doses are administered 2 months apart and the third dose is administered 6-8 months after the second dose.

TENIVAC may be used to complete the primary immunization series for tetanus and diphtheria, following one or two doses of Diphtheria and Tetanus Toxoids and Pertussis Vaccine Adsorbed (whole-cell DTP), Diphtheria and Tetanus Toxoids and Acellular Pertussis Vaccine Adsorbed (DTaP), and/or Diphtheria and Tetanus Toxoids Adsorbed (DT). However, the safety and efficacy of TENIVAC in such regimens have not been evaluated.

2.2 Routine Booster Immunization

TENIVAC may be used for routine booster immunization against tetanus and diphtheria in persons 7 years of age and older. Routine booster immunization against tetanus and diphtheria is recommended in children 11-12 years of age and every 10 years thereafter.

2.3 Diphtheria Prophylaxis for Case Contacts

TENIVAC may be used for post-exposure diphtheria prophylaxis in persons 7 years of age and older who have not completed primary vaccination, whose vaccination status is unknown, or who have not been vaccinated with diphtheria toxoid within the previous 5 years. Consult recommendations of the Advisory Committee on Immunization Practices for additional interventions for diphtheria prophylaxis in close contacts of diphtheria patients. (1)

2.4 Tetanus Prophylaxis in Wound Management

For active tetanus immunization in wound management of patients 7 years of age and older, a preparation containing tetanus and diphtheria toxoids is preferred instead of single-antigen tetanus toxoid to enhance diphtheria protection. (1) TENIVAC is approved for wound management of patients 7 years of age and older.

The need for active immunization with a tetanus toxoid-containing preparation, with or without passive immunization with Tetanus Immune Globulin (TIG) (Human) depends on both the condition of the wound and the patient's vaccination history. (See Table 1.)

When indicated, TIG (Human) should be administered at a separate site, with a separate needle and syringe, according to the manufacturer's package insert. If a contraindication to using tetanus toxoid-containing preparations exists in a person who has not completed a primary immunizing course of tetanus toxoid and other than a clean, minor wound is sustained, only passive immunization with TIG (Human) should be given. (1)

Table 1: Guide for use of Tetanus and Diphtheria Toxoids Adsorbed (Td) for Tetanus Prophylaxis in Routine Wound Management in Persons 7 Years of Age and Older
History of Adsorbed Tetanus Toxoid (Doses) | Clean, Minor Wounds |  | All Other Wounds [Such as, but not limited to, wounds contaminated with dirt, puncture wounds and traumatic wounds.]
History of Adsorbed Tetanus Toxoid (Doses) | Td | TIG | Td | TIG
Unknown or < three | Yes | No | Yes | Yes
≥ Three [If only three doses of fluid tetanus toxoid have been received, then a fourth dose of toxoid, preferably an adsorbed toxoid should be given.] | No [Yes, if >10 years since last dose.] | No | No [Yes, if >5 years since last dose. (More frequent boosters are not needed and can accentuate side effects.)] | No

2.5 Administration

Just before use, shake the single-dose vial or syringe well until a uniform, white, cloudy suspension results. Parenteral drug products should be inspected visually for particulate matter and discoloration prior to administration, whenever solution and container permit. If these conditions exist, the product should not be administered.

Administer the 0.5 mL dose of TENIVAC intramuscularly. Discard unused portion.

The preferred site is the deltoid muscle. The vaccine should not be injected into the gluteal area or areas where there may be a major nerve trunk.

Do not administer this product intravenously or subcutaneously.

TENIVAC should not be combined through reconstitution or mixed with any other vaccine.

3 DOSAGE FORMS AND STRENGTHS

TENIVAC is a suspension for injection available in 0.5 mL single-dose vials or syringes. [See Description (11).]

4 CONTRAINDICATIONS

4.1 Hypersensitivity

A severe allergic reaction (e.g., anaphylaxis) after a previous dose of TENIVAC or any other tetanus toxoid or diphtheria toxoid-containing vaccine or any other component of this vaccine is a contraindication to administration of TENIVAC. [See Description (11).] Because of uncertainty as to which component of the vaccine may be responsible, none of the components should be administered. Alternatively, such individuals may be referred to an allergist for evaluation if further immunizations are to be considered.

5 WARNINGS AND PRECAUTIONS

5.1 Management of Acute Allergic Reactions

Epinephrine hydrochloride solution (1:1,000) and other appropriate agents and equipment must be available for immediate use in case an anaphylactic or acute hypersensitivity reaction occurs.

5.2 Latex

The tip caps of the TENIVAC prefilled syringes may contain natural rubber latex, which may cause allergic reactions in latex sensitive individuals.

5.3 Frequency of Administration

More frequent doses of TENIVAC than described in Section 2, Dosage and Administration, may be associated with increased incidence and severity of adverse reactions. [See Dosage and Administration (2.1, 2.2, 2.3, 2.4).]

5.4 Arthus Reactions

Persons who experienced an Arthus-type hypersensitivity reaction following a prior dose of a tetanus toxoid-containing vaccine usually have high serum tetanus antitoxin levels and should not receive TENIVAC more frequently than every 10 years, even for tetanus prophylaxis as part of wound management.

5.5 Guillain-Barré Syndrome and Brachial Neuritis

A review by the Institute of Medicine found evidence for a causal relation between tetanus toxoid and both brachial neuritis and Guillain-Barré syndrome. (2) If Guillain-Barré syndrome occurred within 6 weeks of receipt of prior vaccine containing tetanus toxoid, the decision to give TENIVAC or any vaccine containing tetanus toxoid should be based on careful consideration of the potential benefits and possible risks.

5.6 Limitations of Vaccine Effectiveness

Vaccination with TENIVAC may not protect all individuals.

5.7 Altered Immunocompetence

If TENIVAC is administered to immunocompromised persons, including persons receiving immunosuppressive therapy, the expected immune response may not be obtained. [See Drug Interactions (7.3).]

5.8 Syncope

Syncope (fainting) has been reported following vaccination with TENIVAC. Procedures should be in place to avoid injury from fainting.

6 ADVERSE REACTIONS

6.1 Clinical Trials Experience

Because clinical trials are conducted under widely varying conditions, adverse reaction rates observed in the clinical trials of a vaccine cannot be directly compared to rates in the clinical trials of another vaccine and may not reflect the rates observed in practice. The adverse reaction information from clinical trials does, however, provide a basis for identifying the adverse events that appear to be related to vaccine use and for approximating rates of those events.

In a primary immunization study conducted in Canada, 18 participants, 8 of whom were 6 to 9 years of age and 10 of whom were 17 to 56 years of age, received three doses of TENIVAC. In four booster immunization studies conducted in either the US or Canada, TENIVAC was administered to 3,723 participants overall, ranging in age from 11 to 93 years.

In one of these studies, a US multi-center booster immunization study (TDC01), 2,250 adolescents and adults ages 11-59 years of age received TENIVAC in an open-label design and adults 60 years of age and over were randomized to receive either TENIVAC (N = 700) or DECAVAC (Td manufactured by Sanofi Pasteur Inc.) (N = 701). Vaccine assignment for participants ≥60 years of age was unblinded to pharmacists and vaccination nurses, but was blinded to other study personnel and participants. Among participants who received TENIVAC, overall, 80.4% were Caucasian, 3.3% Black, 5.1% Hispanic, 4.5% Asian and 6.6% other races. Among participants ≥60 years of age, the racial distribution was similar for the TENIVAC and DECAVAC groups. Among participants who received TENIVAC, the proportion of participants who were female varied by age group (44.4% of participants 11-18 years of age, 70.1% of participants 19-59 years of age and 62.4% of participants ≥60 years of age). Among participants ≥60 years of age who received DECAVAC, 57.6% were female. Nearly all (99.8%) enrolled participants and all participants in the per-protocol immunogenicity population had a reported or documented history of previous immunization against tetanus and diphtheria and, by report, had not received a vaccine containing tetanus or diphtheria toxoid within 5 years prior to enrollment.

In the US multi-center booster immunization study, solicited injection site reactions and systemic adverse events were monitored on diary cards for a subset of participants 11-59 years of age and for all participants ≥60 years of age. The incidence and severity of solicited injection site reactions and selected solicited systemic adverse events that occurred within 3 days following vaccination are shown in Table 2.

Table 2: Frequency and Severity of Selected Solicited Adverse Events Within 0–3 Days Following TENIVAC or DECAVAC in a US Study
 | TENIVAC |  |  | DECAVAC
 | Adolescents 11 to 18 years N = 491–492 % | Adults 19 to 59 years N = 247 % | Adults ≥60 years N = 688–695 % | Adults ≥60 years N = 686–693 %
Injection Site Adverse Reactions
Pain
Any | 80.1 | 74.9 | 35.3 | 29.4
Moderate [Moderate: interfered with activities, but did not require medical care or absenteeism.] | 15.0 | 18.2 | 2.9 | 2.3
Severe [Severe: incapacitating, unable to perform usual activities, may have/or required medical care or absenteeism.] | 0.2 | 0.4 | 0.6 | 0.7
Redness
Any | 25.6 | 15.8 | 18.1 | 18.0
≥35 mm to <50 mm | 1.2 | 2.4 | 0.7 | 1.3
≥50 mm | 0.4 | 0.4 | 2.3 | 1.9
Swelling
Any | 15.0 | 17.0 | 12.1 | 13.0
≥35 mm to <50 mm | 1.2 | 2.8 | 1.0 | 1.3
≥50 mm | 1.8 | 2.8 | 1.7 | 1.3
Systemic Adverse Events
Fever
≥37.5°C | 4.3 | 5.7 | 2.5 | 3.8
≥38.0°C to <39°C | 0.8 | 1.6 | 0.6 | 0.9
≥39°C | 0.0 | 0.0 | 0.1 | 0.1
Headache
Any | 23.0 | 25.1 | 11.7 | 10.8
Moderate | 4.3 | 7.3 | 1.6 | 1.4
Severe | 0.6 | 0.8 | 0.0 | 0.3
Muscle Weakness
Any | 32.3 | 17.4 | 4.9 | 5.9
Moderate | 7.3 | 3.2 | 1.3 | 1.0
Severe | 0.6 | 0.4 | 0.1 | 0.1
Malaise
Any | 14.5 | 17.0 | 8.9 | 8.8
Moderate | 3.5 | 3.2 | 2.4 | 1.2
Severe | 0.8 | 0.4 | 0.1 | 0.4
Pain in Joints
Any | 15.7 | 10.9 | 8.5 | 7.4
Moderate | 2.8 | 1.6 | 2.2 | 1.4
Severe | 0.6 | 0.4 | 0.1 | 0.0

In the US booster immunization study, among participants ≥60 years of age, 7 (1.0%) participants in the TENIVAC group and 10 (1.4%) participants in the DECAVAC group experienced a serious adverse event within 30 days following vaccination. During this period, 2 (0.3%) participants 19-59 years of age and no participants 11-18 years of age experienced a serious adverse event following TENIVAC. Serious adverse events within 30 days following TENIVAC included localized infection, asthma, colonic polyp, cellulitis, angina pectoris, hip and wrist fracture, cholecystitis, chest pain and cerebrovascular accident.

There were five deaths reported during the study. All of the reported deaths were in participants ≥60 years of age and occurred >30 days post-vaccination: three in the TENIVAC group (cardiopulmonary arrest; myocardial infarction and septic shock; and unknown cause) and two in the DECAVAC group (myocardial infarction and congestive heart failure; and liver cancer).

In the primary immunization study (N = 18) in which serious adverse events were monitored for 3 days following each vaccination and in three other booster immunization studies in which serious adverse events were monitored for either four days (N = 347) or one month (N = 426) following vaccination, no serious adverse events were reported.

6.2 Postmarketing Experience

The following adverse events have been spontaneously reported during the postmarketing use of TENIVAC. Because these events are reported voluntarily from a population of uncertain size, it is not always possible to reliably estimate their frequency or establish a causal relationship to vaccine exposure.

The following adverse events were included based on severity, frequency of reporting or the strength of causal association to TENIVAC:

- Blood and lymphatic system disorders
  Lymphadenopathy
- Immune system disorders
  Allergic reactions (such as erythematous rash, maculopapular rash, urticaria and pruritus);
  anaphylactic reaction (bronchospasm and angioedema).
- Nervous system disorders
  Paresthesia, dizziness, syncope
  Guillain-Barré syndrome
- Gastrointestinal disorders
  Vomiting
- Musculoskeletal, connective tissue and bone disorders
  Myalgia, pain in extremities
- General disorders and administration site conditions
  Injection site reactions (including inflammation, mass, edema, induration, warmth, pruritus, cellulitis, discomfort)
  Fatigue, edema peripheral

7 DRUG INTERACTIONS

7.1 Concomitant Vaccine Administration

No safety and immunogenicity data are available on the concomitant administration of TENIVAC with other US licensed vaccines.

7.2 Tetanus Immune Globulin (Human)

If passive protection against tetanus is required, TIG (Human) may be administered according to its prescribing information, concomitantly with TENIVAC at a separate site with a separate needle and syringe. [See Dosage and Administration (2.4).]

7.3 Immunosuppressive Treatments

Immunosuppressive therapies, including irradiation, antimetabolites, alkylating agents, cytotoxic drugs and corticosteroids (used in greater than physiologic doses), may reduce the immune response to TENIVAC. [See Warnings and Precautions (5.7).]

8 USE IN SPECIFIC POPULATIONS

8.1 Pregnancy

Risk Summary

All pregnancies have a risk of birth defect, loss, or other adverse outcomes. In the US general population, the estimated background risk of major birth defects and miscarriage in clinically recognized pregnancies is 2% to 4% and 15% to 20%, respectively. There are no adequate and well-controlled studies of TENIVAC administration in pregnant women in the U.S. There are insufficient human data from TENIVAC administered during pregnancy to establish the presence or absence of a vaccine-associated risk.

A developmental toxicity study has been performed in female rabbits administered a single human dose of TENIVAC prior to mating and during gestation. This study revealed no evidence of harm to the fetus due to TENIVAC. (See Animal data)

Data

Animal data

In a developmental toxicity study, female rabbits received a single human dose (0.5 mL) of TENIVAC by intramuscular injection 17 and 10 days prior to mating, and on gestation days 6 and 29. No adverse effects on pre-weaning development up to post-natal day 35 were observed. There were no vaccine-related fetal malformations or variations observed.

8.2 Lactation

It is not known whether TENIVAC components are excreted in human milk. Data are not available to assess the effect of administration of TENIVAC on breastfed infants or on milk production/excretion.

The developmental and health benefits of breastfeeding should be considered along with the mother's clinical need for TENIVAC and any potential adverse effects on the breastfed child from TENIVAC or from the underlying maternal condition. For preventive vaccines, the underlying maternal condition is susceptibility to disease prevented by the vaccine.

8.4 Pediatric Use

TENIVAC is not approved for use in infants and children younger than 7 years of age. Safety and effectiveness of TENIVAC in this age group have not been established.

8.5 Geriatric Use

In one clinical study, (TDC01) 449 participants 65 years of age and over, including 192 participants who were 75 years of age and over received a dose of TENIVAC. A lower proportion of participants 65 years of age and over had a pre-vaccination seroprotective level of antibody to tetanus toxoid and diphtheria toxin compared to adolescents and adults less than 65 years of age. The proportion of participants 65 years of age and over with a seroprotective level of antibody following TENIVAC was marginally lower for tetanus and lower for diphtheria compared to younger participants. In general, rates of solicited adverse events were not higher in participants 65 years of age and over compared to younger participants. [See Adverse Reactions (6), Clinical Pharmacology (12.1), and Clinical Studies (14.2).]

11 DESCRIPTION

TENIVAC, Tetanus and Diphtheria Toxoids Adsorbed, is a sterile isotonic suspension of tetanus and diphtheria toxoids adsorbed on aluminum phosphate.

Each 0.5 mL dose of TENIVAC contains the following active ingredients:

Tetanus Toxoid | 5 Lf
Diphtheria Toxoid | 2 Lf

Other ingredients per 0.5 mL dose include 1.5 mg of aluminum phosphate (0.33 mg of aluminum) as the adjuvant and ≤5.0 mcg of residual formaldehyde.

Clostridium tetani is grown in modified Mueller-Miller casamino acid medium without beef heart infusion. (3) Tetanus toxin is detoxified with formaldehyde and purified by ammonium sulfate fractionation and diafiltration. Corynebacterium diphtheriae is grown in modified Mueller's growth medium. (4) After purification by ammonium sulfate fractionation, diphtheria toxin is detoxified with formaldehyde and diafiltered. Tetanus and diphtheria toxoids are individually adsorbed onto aluminum phosphate.

The adsorbed tetanus and diphtheria toxoids are combined with aluminum phosphate (as adjuvant), sodium chloride and water for injection. This product contains no preservative.

In the guinea pig potency test, the tetanus toxoid component induces at least 2 neutralizing units/mL of serum and the diphtheria toxoid component induces at least 0.5 neutralizing units/mL of serum.

The tip caps of the prefilled syringes may contain natural rubber latex. The vial stoppers do not contain latex.

12 CLINICAL PHARMACOLOGY

12.1 Mechanism of Action

Tetanus

Tetanus is an acute disease caused by an extremely potent neurotoxin produced by C tetani. Protection against disease is due to the development of neutralizing antibodies to tetanus toxin. A serum tetanus antitoxin level of at least 0.01 IU/mL, measured by neutralization assay is considered the minimum protective level. (5) (6) A tetanus antitoxoid level of ≥0.1 IU/mL as measured by the ELISA used in some clinical studies of TENIVAC is considered protective.

Diphtheria

Diphtheria is an acute toxin-mediated disease caused by toxigenic strains of C diphtheriae. Protection against disease is due to the development of neutralizing antibodies to diphtheria toxin. A serum diphtheria antitoxin level of 0.01 IU/mL is the lowest level giving some degree of protection. Antitoxin levels of at least 0.1 IU/mL are generally regarded as protective. (5) A level of at least of 1.0 IU/mL has been associated with long-term protection. (7)

13 NONCLINICAL TOXICOLOGY

13.1 Carcinogenesis, Mutagenesis, Impairment of Fertility

TENIVAC has not been evaluated for carcinogenic or mutagenic potential or impairment of male fertility in animals. Vaccination of female rabbits with TENIVAC had no effects on fertility. [See Use in Specific Populations (8.1)].

14 CLINICAL STUDIES

14.1 Primary Immunization

A three-dose primary immunization series with TENIVAC was evaluated in 17 participants ages 6 to 56 years in a study conducted in Canada. [See Adverse Reactions (6.1).] The first two doses were administered two months apart, followed by a third dose six to eight months after the second dose. Serum tetanus antitoxin levels were measured by an in vivo neutralizing assay and serum diphtheria antitoxin levels were measured by an in vitro neutralizing assay. [See Clinical Pharmacology (12.1).] All 17 participants had serum tetanus and diphtheria antitoxin levels pre-vaccination and 7 days post-vaccination <0.01 IU/mL, consistent with no previous immunization. Four weeks following the second dose, all 17 participants had a serum tetanus antitoxin level >0.1 IU/mL and a serum diphtheria antitoxin level ≥0.01 IU/mL. Four weeks following the third dose, all 17 participants had a serum diphtheria antitoxin level >0.1 IU/mL.

14.2 Booster Immunization

In the US multicenter booster immunization study (TDC01) [see Adverse Reactions (6.1)], the immune response to a dose of TENIVAC was evaluated in an open-label manner in a subset of participants 11 to 59 years of age, and in comparison to DECAVAC in participants ≥60 years of age who were randomized to receive a dose of either TENIVAC or DECAVAC. Tetanus immune responses, measured by ELISA [see Clinical Pharmacology (12.1)] are presented in Table 3. Diphtheria immune responses, measured by a microneutralization assay [see Clinical Pharmacology (12.1)], are presented in Table 4.

Among adults 65 years of age and over who received TENIVAC (N = 419), 94.5% (95% confidence interval 91.9, 96.5) had a post-vaccination tetanus antitoxoid level ≥0.1 IU/mL and 61.1% (95% confidence interval 56.2, 65.8) had a post-vaccination diphtheria antitoxoid level ≥0.1 IU/mL.

Table 3: Tetanus Antitoxoid Levels and Booster Response Rates Following a Dose of TENIVAC, by Age Group, and for Adults ≥60 Years of Age, Compared to DECAVAC, per Protocol Immunogenicity Population
Treatment Group | Age Group | Timing | Percent of Participants With Specified Level of Tetanus Antitoxoid and Booster Response
Treatment Group | Age Group | Timing | ≥0.1 IU/mL % (95% CI) | ≥1.0 IU/mL % (95% CI) | Booster Response [Booster response: If pre-vaccination level ≤0.10 IU/mL, 4-fold increase and post-vaccination level ≥0.10 IU/mL. If pre-vaccination level >0.10 IU/mL and ≤2.7 IU/mL, 4-fold increase. If pre-vaccination level >2.7 IU/mL, 2-fold increase.] % (95% CI)
TENIVAC | Adolescents 11 to 18 years (N = 470) | Pre- | 97.9 (96.1, 99.0) | 48.7 (44.1, 53.3) | -
TENIVAC | Adolescents 11 to 18 years (N = 470) | Post- | 100.0 (99.2, 100) | 99.8 (98.8, 100) | 92.8 (90.0, 94.9)
TENIVAC | Adults 19 to 59 years (N = 237) | Pre- | 97.5 (94.6, 99.1) | 77.6 (71.8, 82.8) | -
TENIVAC | Adults 19 to 59 years (N = 237) | Post- | 100.0 (98.5, 100) | 99.6 (97.7, 100) | 84.0 (78.7, 88.4)
TENIVAC | Adults ≥60 years (N = 661) | Pre- | 76.2 (72.8, 79.4) | 43.7 (39.9, 47.6) | -
TENIVAC | Adults ≥60 years (N = 661) | Post- | 96.1 [TENIVAC non-inferior to DECAVAC [upper limit of 95% CI for difference (DECAVAC minus TENIVAC) <5%].] (94.3, 97.4) | 90.6 [Non-inferiority criteria not prospectively specified for this endpoint.] (88.1, 92.7) | 82.3 [TENIVAC non-inferior to DECAVAC [upper limit of 95% CI for difference (DECAVAC minus TENIVAC) <10%].] (79.2, 85.1)
DECAVAC | Adults ≥60 years (N = 658) | Pre- | 75.2 (71.7, 78.5) | 45.7 (41.9, 49.6) | -
DECAVAC | Adults ≥60 years (N = 658) | Post- | 97.3 (95.7, 98.4) | 91.9 (89.6, 93.9) | 83.7 (80.7, 86.5)
Pre- indicates pre-vaccination bleed.
Post- indicates 26–42 days post-vaccination bleed.

Table 4: Diphtheria Antitoxin Levels and Booster Response Rates Following a Dose of TENIVAC, by Age Group, and for Adults ≥60 Years of Age, Compared to DECAVAC, per Protocol Immunogenicity Population
Treatment Group | Age Group | Timing | Percent of Participants With Specified Level of Diphtheria Antitoxin and Booster Response
Treatment Group | Age Group | Timing | ≥0.01 IU/mL % (95% CI) | ≥0.1 IU/mL % (95% CI) | ≥1.0 IU/mL % (95% CI) | Booster Response [Booster response: If pre-vaccination level ≤0.10 IU/mL, 4-fold increase and post-vaccination level ≥0.10 IU/mL. If pre-vaccination level >0.10 IU/mL and ≤2.56 IU/mL, 4-fold increase. If pre-vaccination level >2.56 IU/mL, 2-fold increase.] % (95% CI)
TENIVAC | Adolescents 11 to 18 years (N = 470) | Pre- | 99.1 (97.8, 99.8) | 78.7 (74.7, 82.3) | 18.5 (15.1, 22.3) | -
TENIVAC | Adolescents 11 to 18 years (N = 470) | Post- | 100.0 (99.2, 100) | 99.8 (98.8, 100) | 98.9 (97.5, 99.7) | 95.7 (93.5, 97.4)
TENIVAC | Adults 19 to 59 years (N = 237) | Pre- | 96.6 (93.5, 98.5) | 73.0 (66.9, 78.5) | 18.6 (13.8, 24.1) | -
TENIVAC | Adults 19 to 59 years (N = 237) | Post- | 99.2 (97.0, 99.9) | 97.5 (94.6, 99.1) | 91.1 (86.8, 94.4) | 89.9 (85.3, 93.4)
TENIVAC | Adults ≥60 years (N = 661) | Pre- | 61.9 (58.1, 65.6) | 29.0 (25.6, 32.7) | 8.5 (6.5, 10.9) | -
TENIVAC | Adults ≥60 years (N = 661) | Post- | 88.0 [Non-inferiority criteria not prospectively specified for this endpoint.] (85.3, 90.4) | 71.1 [TENIVAC non-inferior to DECAVAC [upper limit of 95% CI for difference (DECAVAC minus TENIVAC) <10%].] (67.5, 74.5) | 47.5 (43.6, 51.4) | 65.5 (61.7, 69.1)
DECAVAC | Adults ≥60 years (N = 658) | Pre- | 61.7 (57.9, 65.4) | 32.2 (28.7, 35.9) | 10.5 (8.3, 13.1) | -
DECAVAC | Adults ≥60 years (N = 658) | Post- | 87.4 (84.6, 89.8) | 70.7 (67.0, 74.1) | 45.7 (41.9, 49.6) | 62.9 (59.1, 66.6)
Pre- indicates pre-vaccination bleed.
Post- indicates 26–42 days post-vaccination bleed.

15 REFERENCES

1 CDC. Diphtheria, tetanus and pertussis: recommendations for vaccine use and other preventive measures. Recommendations of the Immunization Practices Advisory Committee (ACIP). MMWR 1991;40(RR-10):1-28.
2 Stratton KR, et al, editors. Adverse events associated with childhood vaccines; evidence bearing on causality. Washington, DC: National Academy Press 1994. p. 67-117.
3 Mueller JH, Miller PA. Variable factors influencing the production of tetanus toxin. J Bacteriol 1954;67(3):271-7.
4 Stainer DW. Production of diphtheria toxin. In: Manclark CR, editor. Proceedings of an informal consultation on the World Health Organization requirements for diphtheria, tetanus, pertussis and combined vaccines. United States Public Health Services, Bethesda, MD. DHHS 91-1174. 1991. p. 7-11.
5 FDA. Department of Health and Human Services (DHHS). Biological products; bacterial vaccines and toxoids; implementation of efficacy review; proposed rule. Fed Reg 1985;50(240):51002-117.
6 Wassilak SGF, et al. Tetanus toxoid. In: Plotkin SA, Orenstein WA, Offit PA, editors. Vaccines. 5th ed. Philadelphia, PA: W.B. Saunders Company; 2008. p. 805-39.
7 Vitek CR and Wharton M. Diphtheria toxoid. In: Plotkin SA, Orenstein WA, Offit PA, editors. Vaccines. 5th ed. Philadelphia, PA: W.B. Saunders Company; 2008. p. 139-56.

16 HOW SUPPLIED/STORAGE AND HANDLING

Single-dose Vial, NDC No. 49281-215-58; in package of 10 vials, NDC No. 49281-215-10. Contains no latex.

Single-dose Syringe, NDC No. 49281-215-88; in package of 10 syringes, NDC No. 49281-215-15. The tip caps of the prefilled syringes may contain natural rubber latex. No other components contain latex.

STORAGE AND HANDLING

TENIVAC should be stored at 2° to 8°C (35° to 46°F). DO NOT FREEZE. Product which has been exposed to freezing should not be used. Do not use after expiration date shown on the label.

17 PATIENT COUNSELING INFORMATION

Before administration of TENIVAC health-care providers should inform the patient, parent or guardian of the benefits and risks of the vaccine and the importance of completing the primary immunization series or receiving recommended booster doses, as appropriate, unless a contraindication to further immunization exists.

The health-care provider should inform the patient, parent or guardian about the potential for adverse reactions that have been temporally associated with TENIVAC or other vaccines containing similar components. The health-care provider should provide the Vaccine Information Statements (VISs) which are required by the National Childhood Vaccine Injury Act of 1986 to be given with each immunization. Patients, parents, or guardians should be instructed to report adverse reactions to their health-care provider.

Manufactured by:
Sanofi Pasteur Limited
Toronto Ontario Canada

Distributed by:
Sanofi Pasteur Inc.
Swiftwater PA 18370 USA

TENIVAC® is a registered trademark of Sanofi Pasteur Limited.

©, 2024, Sanofi Pasteur Limited – All rights reserved

R8-0424 USA

PRINCIPAL DISPLAY PANEL - 0.5 mL Vial Label

7 yrs of age and older
Td

NDC 49281-215-58

Tetanus and
Diphtheria
Toxoids Adsorbed

TENIVAC®

Rx only

single-dose (0.5 mL)
IM only

Sanofi Pasteur Limited

PRINCIPAL DISPLAY PANEL - 10 Vial Package

NDC 49281-215-10
Td

Tetanus and
Diphtheria Toxoids
Adsorbed

10 single-dose vials
0.5 mL each

Rx only

TENIVAC®

For persons 7 years
of age and older.

SANOFI PASTEUR

PRINCIPAL DISPLAY PANEL - 0.5 mL Syringe Label

NDC 49281-215-88

single-dose (0.5 mL)
Td

Tetanus and Diphtheria
Toxoids Adsorbed
TENIVAC®
7 yrs of age and older
Sanofi Pasteur Limited

IM only
Rx only

PRINCIPAL DISPLAY PANEL - 10 Syringe Package

Td

NDC 49281-215-15

10 single-dose
prefilled syringes
0.5 mL each

Tetanus and
Diphtheria Toxoids
Adsorbed

Rx only

TENIVAC®

For persons 7 years
of age and older

SANOFI PASTEUR